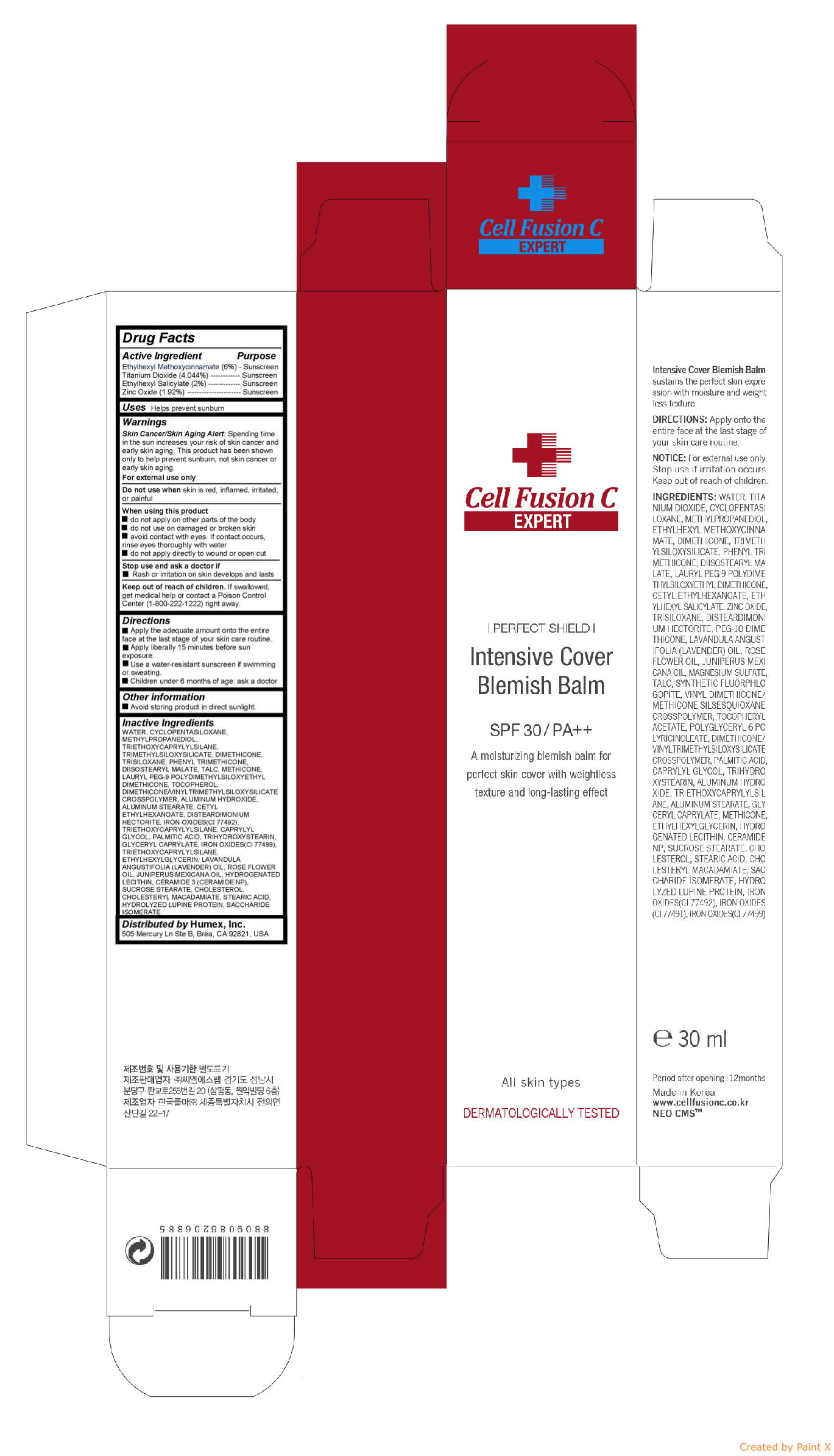 DRUG LABEL: Intensive Cover Blemish Balm
NDC: 52554-1113 | Form: CREAM
Manufacturer: CMS LAB Inc.
Category: otc | Type: HUMAN OTC DRUG LABEL
Date: 20171111

ACTIVE INGREDIENTS: OCTINOXATE 1.8 g/30 mL; Titanium Dioxide 1.2132 g/30 mL; OCTISALATE 0.6 g/30 mL; Zinc Oxide 0.576 g/30 mL
INACTIVE INGREDIENTS: WATER; CYCLOMETHICONE 5; METHYLPROPANEDIOL; TRIETHOXYCAPRYLYLSILANE; DIMETHICONE; TRISILOXANE; PHENYL TRIMETHICONE; DIISOSTEARYL MALATE; TALC; METHICONE (20 CST); LAURYL PEG-9 POLYDIMETHYLSILOXYETHYL DIMETHICONE; TOCOPHEROL; ALUMINUM HYDROXIDE; ALUMINUM STEARATE; CETYL ETHYLHEXANOATE; DISTEARDIMONIUM HECTORITE; FERRIC OXIDE RED; PEG-10 DIMETHICONE (600 CST)

Intensive Cover Blemish Balm

Active ingredients

Ethylhexyl Methoxycinnamate (6%)

Titanium Dioxide (4.044%)

Ethylhexyl Salicylate (2%)

Zinc Oxide (1.92%)

Purpose

Sunscreen

Uses

Helps prevent sunburn

Warnings

Skin Cancer/Skin Aging Alert: Spending time in the sun increases your risk of skin cancer and early skin aging. This product has been shown only to help prevent sunburn, not skin cancer or early skin aging.

For external use only

Do not use when skin is red, inflamed, irritated, or painful

When using this product do not apply on other parts of the body do not use on damaged or broken skin avoid contact with eyes. If contact occurs, rinse eyes thoroughly with water do not apply directly to wound or open cut

Stop use and ask a doctor if Rash or irritation on skin develops and lasts

Keep out of reach of children

If swallowed, get medical help or contact a Poison Control Center (1-800-222-1222) right away.

Directions

- Apply the adequate amount onto the entire face at the last stage of your skin care routine.

- Apply liberally 15 minutes before sun exposure.

- Use a water-resistant sunscreen if swimming or sweating.

- Children under 6 months of age: ask a doctor

Inactive ingredients

WATER, CYCLOPENTASILOXANE, METHYLPROPANEDIOL, TRIETHOXYCAPRYLYLSILANE, TRIMETHYLSILOXYSILICATE, DIMETHICONE, TRISILOXANE, PHENYL TRIMETHICONE, DIISOSTEARYL MALATE, TALC, METHICONE, LAURYL PEG-9 POLYDIMETHYLSILOXYETHYL DIMETHICONE, TOCOPHEROL, DIMETHICONE/VINYLTRIMETHYLSILOXYSILICATE CROSSPOLYMER, ALUMINUM HYDROXIDE, ALUMINUM STEARATE, CETYL ETHYLHEXANOATE, DISTEARDIMONIUM HECTORITE, IRON OXIDES(CI 77492), TRIETHOXYCAPRYLYLSILANE, CAPRYLYL GLYCOL, PALMITIC ACID, TRIHYDROXYSTEARIN, GLYCERYL CAPRYLATE, IRON OXIDES(CI 77499), TRIETHOXYCAPRYLYLSILANE, ETHYLHEXYLGLYCERIN, LAVANDULA ANGUSTIFOLIA (LAVENDER) OIL, ROSE FLOWER OIL, JUNIPERUS MEXICANA OIL, HYDROGENATED LECITHIN, CERAMIDE 3 (CERAMIDE NP), SUCROSE STEARATE, CHOLESTEROL, CHOLESTERYL MACADAMIATE, STEARIC ACID, HYDROLYZED LUPINE PROTEIN, SACCHARIDE ISOMERATE